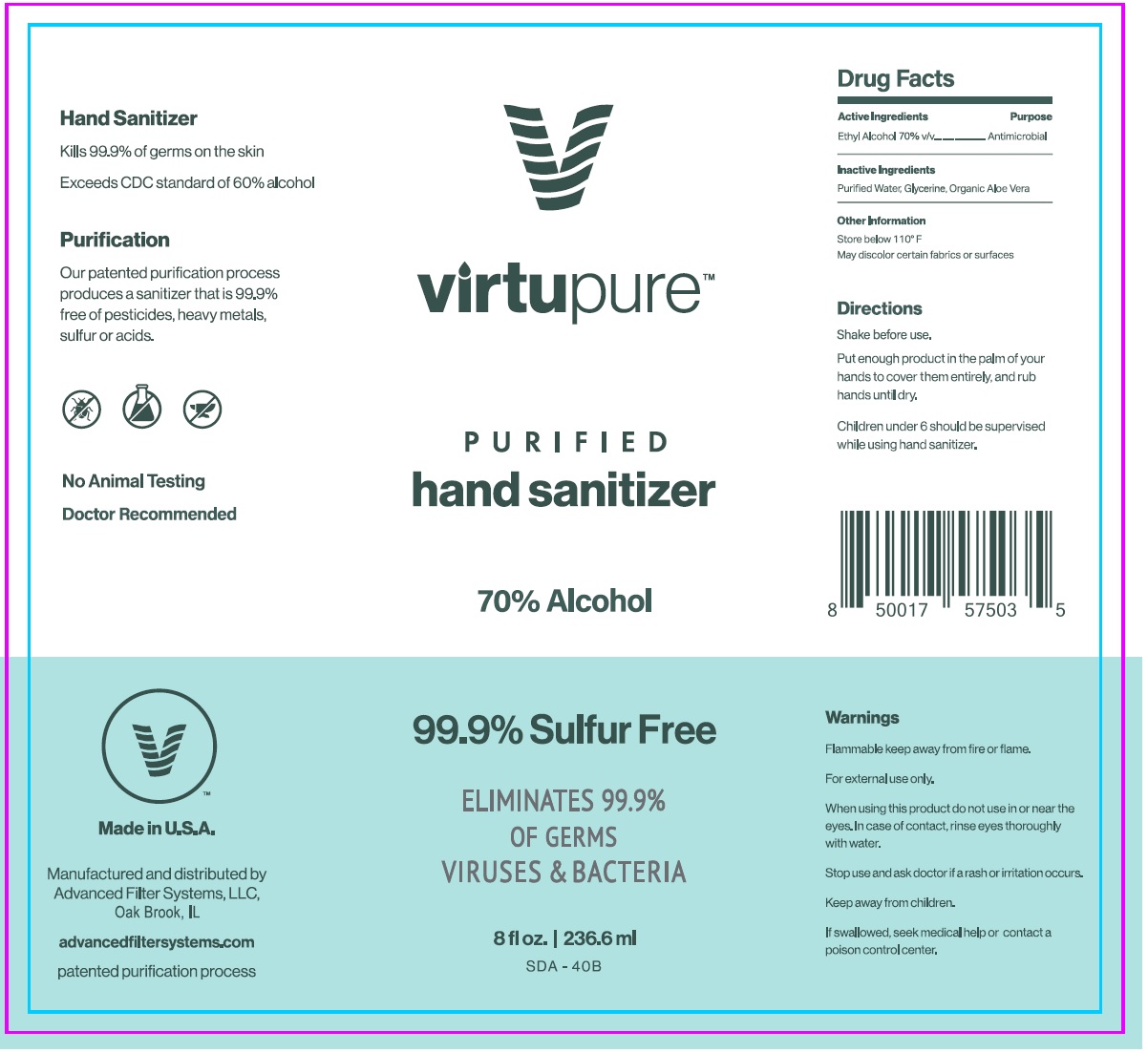 DRUG LABEL: VirtuPure
NDC: 77787-070 | Form: LIQUID
Manufacturer: Advanced Filter Systems LLC
Category: otc | Type: HUMAN OTC DRUG LABEL
Date: 20200626

ACTIVE INGREDIENTS: ALCOHOL 70 mL/100 mL
INACTIVE INGREDIENTS: WATER; GLYCERIN; ALOE VERA LEAF

Virtupure™ PURIFIED hand sanitizer

Active Ingredients

Ethyl Alcohol 70% v/v

Purpose

Antimicrobial

INDICATIONS AND USAGE

Use Hand sanitizer to help reduce bacteria on the skin.

Warnings

Flammable keep away from fire or flame.

For external use only.

When using this product do not use in or near the eyes. In case of contact, rinse eyes thoroughly with water.

Stop use and ask doctor if a rash or irritation occurs.

Keep away from children.

If swallowed, seek medical help or contact a poison control center.

Directions

Shake before use.

Put enough product in the palm of your hands to cover them entirely, and rub hands until dry.

Children under 6 should be supervised while using hand sanitizer.

Other Information

Store below 110° F

May discolor certain fabrics or surfaces

Inactive Ingredients

Purified Water, Glycerine, Organic Aloe Vera

99.9% Sulfur Free

ELIMINATES 99.9% OF GERMS

VIRUS & BACTERIA

Hand Sanitizer

Kills 99.9% of germs on the skin

Exceeds CDC standard of 60% alcohol

Purification

Our patented purification process produces a sanitizer that is 99.9% free of pesticides, heavy metals, sulfur or acids.

No Animal Testing

Doctor Recommended

Made in U.S.A.

Manufactured and distributed by

Advanced Filter Systems, LLC,

Oak Brook, IL

advancedfiltersystems.com

patented purification process